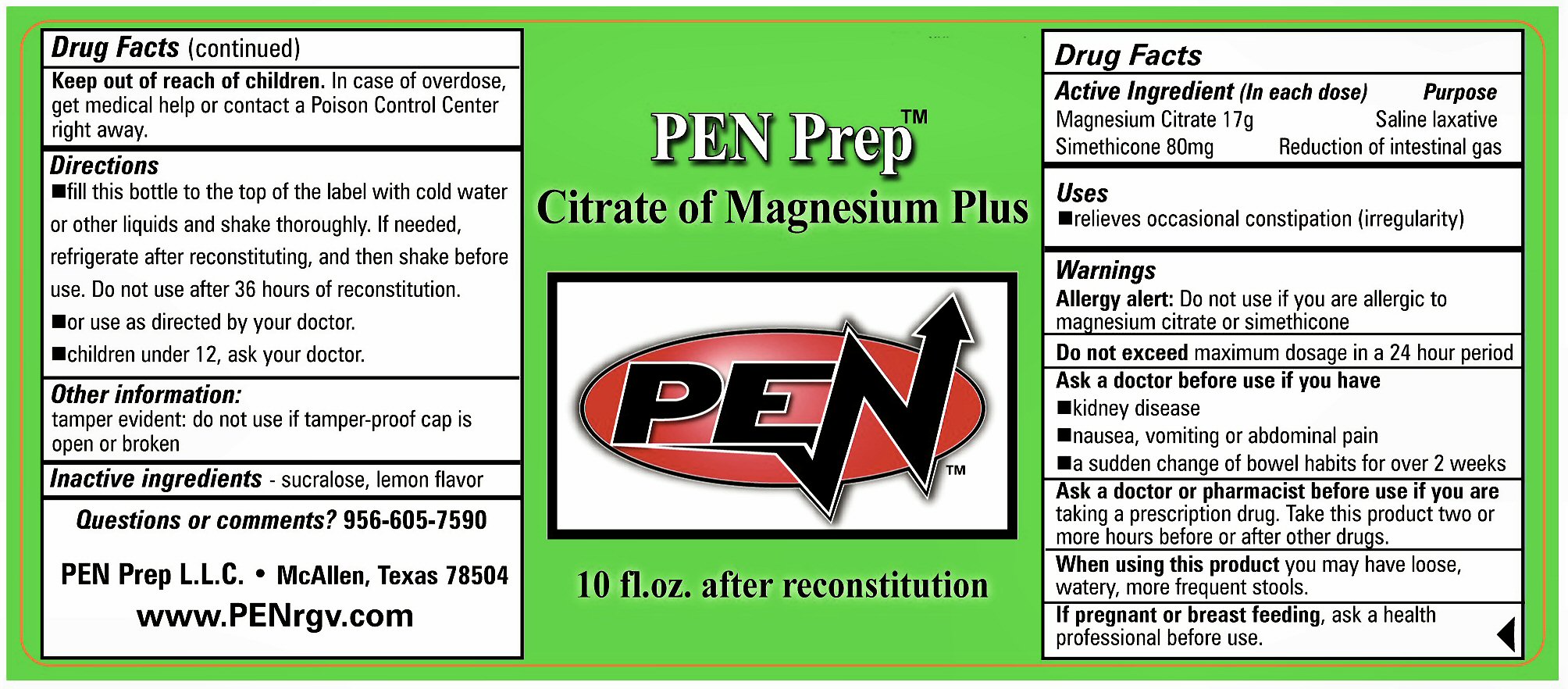 DRUG LABEL: PEN Prep Plus
NDC: 76334-002 | Form: POWDER, FOR SOLUTION
Manufacturer: PEN Prep LLC
Category: otc | Type: HUMAN OTC DRUG LABEL
Date: 20111122

ACTIVE INGREDIENTS: MAGNESIUM CITRATE 17 g/100 g; DIMETHICONE  .08 g/100 g
INACTIVE INGREDIENTS: SUCRALOSE

OTC ACTIVE INGREDIENT SECTION

DRUG FACTS ACTIVE INGREGIENT (IN EACH DOSE) MAGNESIUM CITRATE 17 G SIMETHICONE 80 MG

INACTIVE INGREDIENT SECTION

SUCRALOSE, LEMON FLAVOR

INDICATIONS AND USES

RELIEVES OCCASIONAL CONSTIPATION (IRREGULARITY)

DOSAGE AND ADMINISTRATION SECTION

FILL THIS BOTTLE TO THE TOP OF THE LABEL WITH COLD WATER OR OTHER LIQUIDS AND SHAKE THOROUGHLY. IF NEEDED, REFRIGERATE AFTER RECONSTITUTING, AND THEN SHAKE BEFORE USE. DO NOT USE AFTER 36 HOURS OF RECONSTITUTION. OR USE AS DIRECTED BY YOUR DOCTOR. CHILDREN UNDER 12, ASK YOUR DOCTOR.

KEEP OUT OF REACH OF CHILDREN SECTION

KEEP OUT OF REACH OF CHILDREN. IN CASE OF OVERDOSE, GET MEDICAL HELP OR CONTACT A POISON CONTROL CENTER RIGHT AWAY.

WARNINGS SECTION

WARNINGS: ALLERGY ALERT: DO NOT USE IF YOU ARE ALLERGIC TO MAGNESIUM CITRATE OR SIMETHICONE. DO NOT EXCEED MAXIMUM DOSE IN A 24 HOUR PERIOD. ASK A DOCTOR BEFORE USE IF YOU HAVE KIDNEY DISEASE NAUSEA, VOMITING OR ABDOMINAL PAIN A SUDDEN CHANGE OF BOWEL HABITS FOR OVER 2 WEEKS
ASK A DOCTOR OR PHARMACIST BEFORE USE IF YOU ARE TAKING A PRESCRIPTION DRUG. TAKE THIS PRODUCT TWO OR MORE HOURS BEFORE OR AFTER OTHER DRUDS. WHEN USING THIS PRODUCT YOU MAY HAVE LOOSE, WATERY, MORE FREQUENT STOOLS.

PREGNANCY OR BREAST FEEDING SECTION

IF PREGNANT OR BREAST FEEDING, ASK A HEALTH PROFESSIONAL BEFORE USE.

PURPOSE SECTION

SALINE LAXATIVE REDUCTION OF INTESTINAL GAS

PACKAGE LABEL PRINCIPAL DISPLAY PANEL

PEN PREP TM CITRATE OF MAGNESIUM PLUS 10 FL. OZ. AFTER RECONSTITUTION
OTHER INFORMATION: TAMPER EVIDENT: DO NOT USE IF TAMPER-PROOF CAP IS OPEN OR BROKEN.
QUESTIONS OR COMMENTS? 956-605-7590 PEN PREP L.L.C. MCALLEN, TEXAS 78504 WWW.PENRGV.COM